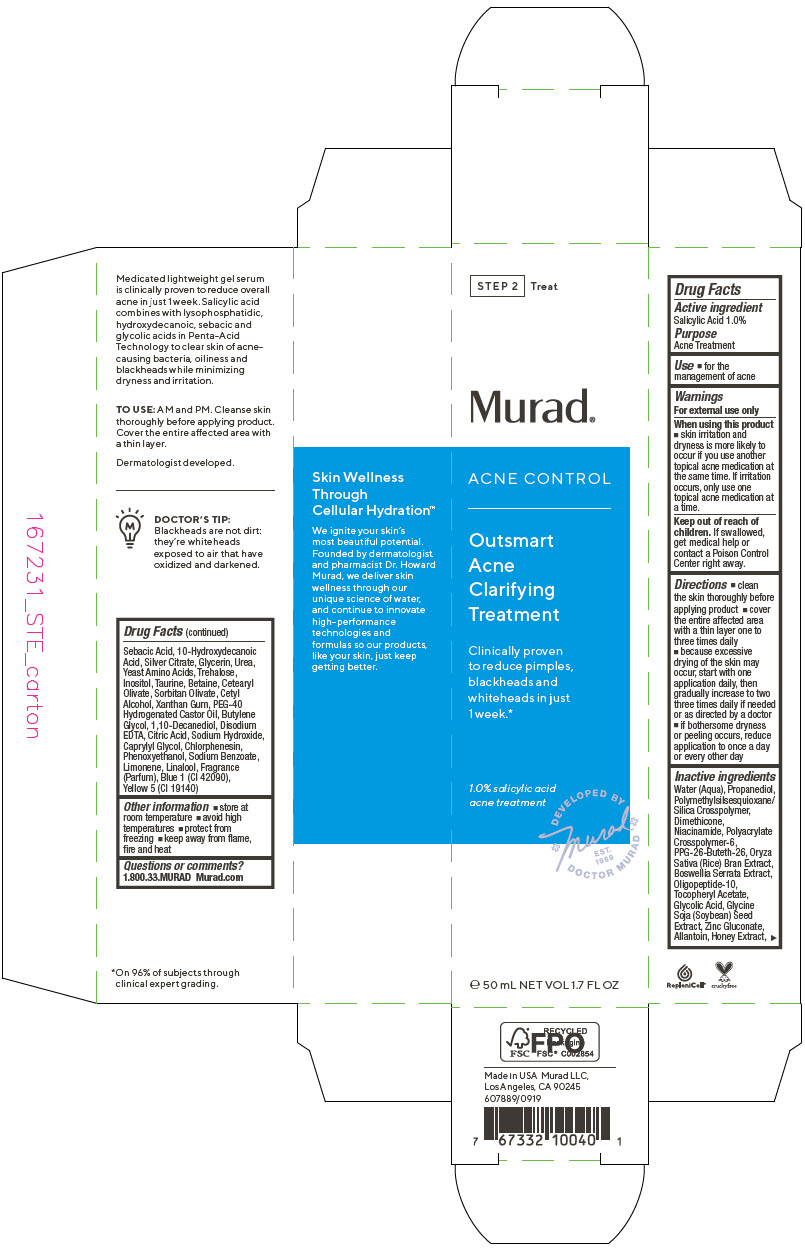 DRUG LABEL: Acne Control Outsmart Acne Clarifying Treatment
NDC: 70381-116 | Form: SOLUTION
Manufacturer: Murad, LLC
Category: otc | Type: HUMAN OTC DRUG LABEL
Date: 20210706

ACTIVE INGREDIENTS: SALICYLIC ACID 1 g/100 mL
INACTIVE INGREDIENTS: WATER; PROPANEDIOL; POLYMETHYLSILSESQUIOXANE (4.5 MICRONS); DIMETHICONE; NIACINAMIDE; AMMONIUM ACRYLOYLDIMETHYLTAURATE, DIMETHYLACRYLAMIDE, LAURYL METHACRYLATE AND LAURETH-4 METHACRYLATE COPOLYMER, TRIMETHYLOLPROPANE TRIACRYLATE CROSSLINKED (45000 MPA.S); PPG-26-BUTETH-26; RICE BRAN; INDIAN FRANKINCENSE; OLIGOPEPTIDE-10; .ALPHA.-TOCOPHEROL ACETATE; GLYCOLIC ACID; SOYBEAN; ZINC GLUCONATE; ALLANTOIN; HONEY; SEBACIC ACID; 10-HYDROXYDECANOIC ACID; SILVER CITRATE; GLYCERIN; UREA; AMINO ACIDS, SOURCE UNSPECIFIED; TREHALOSE; INOSITOL; TAURINE; BETAINE; CETEARYL OLIVATE; SORBITAN OLIVATE; CETYL ALCOHOL; XANTHAN GUM; POLYOXYL 40 HYDROGENATED CASTOR OIL; BUTYLENE GLYCOL; 1,10-DECANEDIOL; EDETATE DISODIUM ANHYDROUS; CITRIC ACID MONOHYDRATE; SODIUM HYDROXIDE; CAPRYLYL GLYCOL; CHLORPHENESIN; PHENOXYETHANOL; SODIUM BENZOATE; LIMONENE, (+)-; LINALOOL, (+/-)-; FD&C BLUE NO. 1; FD&C YELLOW NO. 5

Acne Control Outsmart Acne Clarifying Treatment

Drug Facts

Active ingredient

Salicylic Acid 1.0%

Purpose

Acne Treatment

Use

- for the management of acne

Warnings

For external use only

When using this product

- skin irritation and dryness is more likely to occur if you use another topical acne medication at the same time. If irritation occurs, only use one topical acne medication at a time.

Keep out of reach of children. If swallowed, get medical help or contact a Poison Control Center right away.

Directions

- clean the skin thoroughly before applying product
- cover the entire affected area with a thin layer one to three times daily
- because excessive drying of the skin may occur, start with one application daily, then gradually increase to two three times daily if needed or as directed by a doctor
- if bothersome dryness or peeling occurs, reduce application to once a day or every other day

Inactive ingredients

Water (Aqua), Propanediol, Polymethylsilsesquioxane/Silica Crosspolymer, Dimethicone, Niacinamide, Polyacrylate Crosspolymer-6, PPG-26-Buteth-26, Oryza Sativa (Rice) Bran Extract, Boswellia Serrata Extract, Oligopeptide-10, Tocopheryl Acetate, Glycolic Acid, Glycine Soja (Soybean) Seed Extract, Zinc Gluconate, Allantoin, Honey Extract, Sebacic Acid, 10-Hydroxydecanoic Acid, Silver Citrate, Glycerin, Urea, Yeast Amino Acids, Trehalose, Inositol, Taurine, Betaine, Cetearyl Olivate, Sorbitan Olivate, Cetyl Alcohol, Xanthan Gum, PEG-40 Hydrogenated Castor Oil, Butylene Glycol, 1,10-Decanediol, Disodium EDTA, Citric Acid, Sodium Hydroxide, Caprylyl Glycol, Chlorphenesin, Phenoxyethanol, Sodium Benzoate, Limonene, Linalool, Fragrance (Parfum), Blue 1 (CI 42090), Yellow 5 (CI 19140)

Other information

- store at room temperature
- avoid high temperatures
- protect from freezing
- keep away from flame, fire and heat

Questions or comments?

1.800.33.MURAD
Murad.com

PRINCIPAL DISPLAY PANEL - 50 mL Tube Carton

STEP 2
Treat

Murad®

ACNE CONTROL

Outsmart
Acne
Clarifying
Treatment

Clinically proven
to reduce pimples,
blackheads and
whiteheads in just
1 week.*

1.0% salicylic acid
acne treatment

DEVELOPED BY
+Murad+
EST.
1989
DOCTOR MURAD

℮ 50 mL NET VOL 1.7 FL OZ